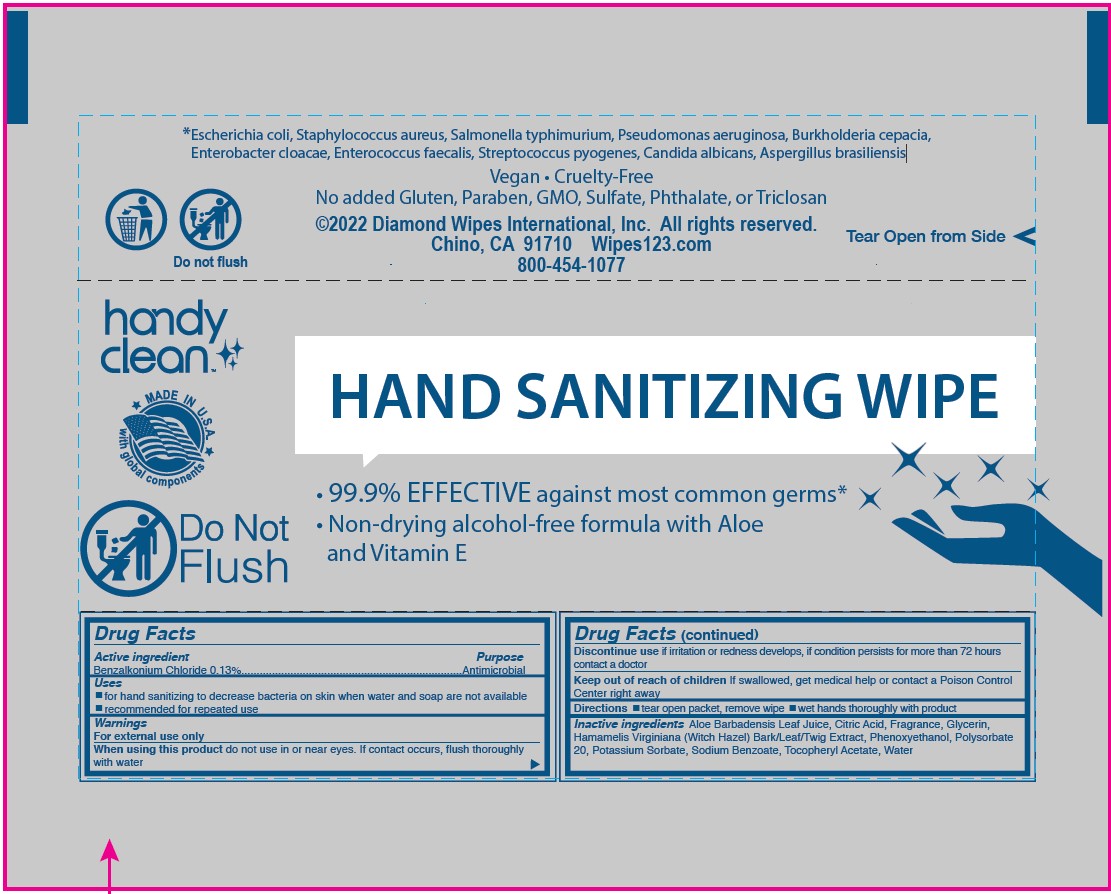 DRUG LABEL: ANTISEPTIC WIPE
NDC: 64709-105 | Form: CLOTH
Manufacturer: Diamond Wipes International
Category: otc | Type: HUMAN OTC DRUG LABEL
Date: 20231130

ACTIVE INGREDIENTS: BENZALKONIUM CHLORIDE 13 g/100 g
INACTIVE INGREDIENTS: CITRIC ACID MONOHYDRATE; HAMAMELIS VIRGINIANA TOP; GLYCERIN; WATER; PHENOXYETHANOL; POLYSORBATE 20; ALOE VERA LEAF; POTASSIUM SORBATE; SODIUM BENZOATE; .ALPHA.-TOCOPHEROL ACETATE

HAND SANITIZING WIPE

Active Ingredient

Benzalkonium Chloride 0.13%

Purpose

Antimicrobial

Uses

■ for hand sanitizing to decrease bacteria on skin when water and soap are not available

■ recommended for repeated use

Warnings

For external use only

When using this product do not use in or near eyes. If contact occurs, flush thoroughly with water

Discontinue use if irritation or redness develops, if condition persists for more than 72 hours contact a doctor

Keep out of reach of children If swallowed, get medical help or contact a Poison Control Center right away

Directions

■ tear open packet, remove wipe ■ wet hands thoroughly with product

Inactive ingredients

Aloe Barbadensis Leaf Juice, Citric Acid, Fragrance, Glycerin,

Hamamelis Virginiana (Witch Hazel) Bark/Leaf/Twig Extract, Phenoxyethanol, Polysorbate

20, Potassium Sorbate, Sodium Benzoate, Tocopheryl Acetate, Water

Label

*Escherichia coli, Staphylococcus aureus, Salmonella typhimurium, Pseudomonas aeruginosa, Burkholderia cepacia,
Enterobacter cloacae, Enterococcus faecalis, Streptococcus pyogenes, Candida albicans, Aspergillus brasiliensis

Vegan • Cruelty-Free
No added Gluten, Paraben, GMO, Sulfate, Phthalate, or Triclosan

©2022 Diamond Wipes International, Inc. All rights reserved.
Chino, CA 91710 Wipes123.com

800-454-1077

Do not flush Tear Open from Side

HAND SANITIZING WIPE

• 99.9% EFFECTIVE against most common germs*
• Non-drying alcohol-free formula with Aloe and Vitamin E

handy clean

MAKE IN U.S.A. with global components

Do Not Flush

Drug Facts
Active ingredient Purpose
Benzalkonium Chloride 0.13%........................................................................Antimicrobial
Uses
■ for hand sanitizing to decrease bacteria on skin when water and soap are not available
■ recommended for repeated use

Warnings
For external use only
When using this product do not use in or near eyes. If contact occurs, flush thoroughly with water

Drug Facts (continued)

Discontinue use if irritation or redness develops, if condition persists for more than 72 hours
contact a doctor
Keep out of reach of children If swallowed, get medical help or contact a Poison Control
Center right away

Directions ■ tear open packet, remove wipe ■ wet hands thoroughly with product

Inactive ingredients Aloe Barbadensis Leaf Juice, Citric Acid, Fragrance, Glycerin,
Hamamelis Virginiana (Witch Hazel) Bark/Leaf/Twig Extract, Phenoxyethanol, Polysorbate
20, Potassium Sorbate, Sodium Benzoate, Tocopheryl Acetate, Water